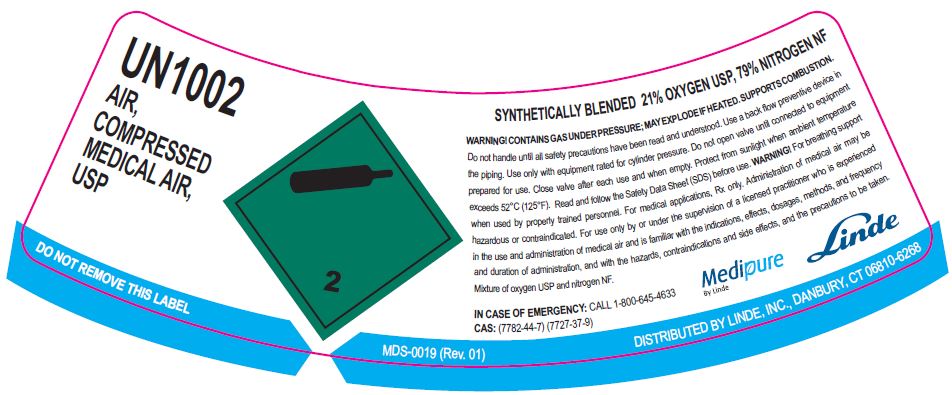 DRUG LABEL: Air
NDC: 11324-006 | Form: GAS
Manufacturer: Linde Puerto Rico B.V.
Category: prescription | Type: HUMAN PRESCRIPTION DRUG LABEL
Date: 20251231

ACTIVE INGREDIENTS: OXYGEN 210 mL/1 L
INACTIVE INGREDIENTS: NITROGEN 790 mL/1 L

Air USP Gurabo